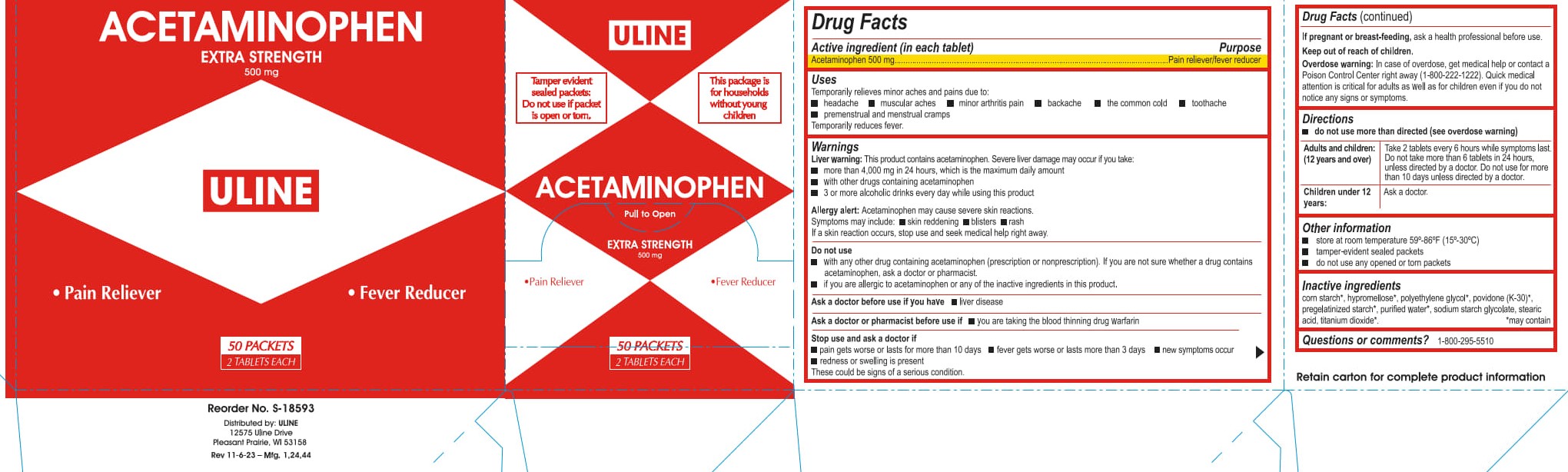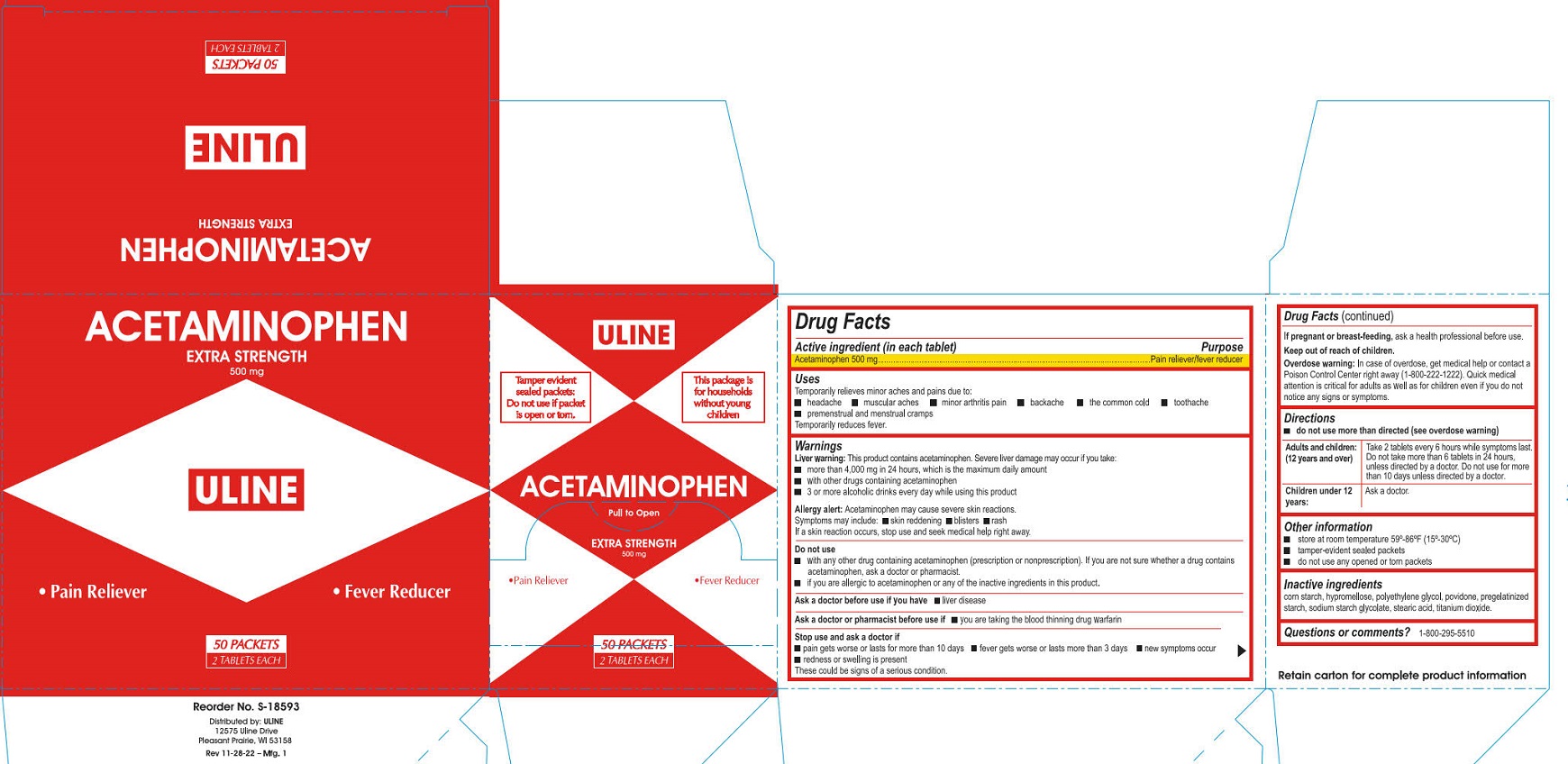 DRUG LABEL: Uline Acetaminophen Extra Strength
NDC: 69790-173 | Form: TABLET, FILM COATED
Manufacturer: Uline
Category: otc | Type: HUMAN OTC DRUG LABEL
Date: 20250909

ACTIVE INGREDIENTS: ACETAMINOPHEN 500 mg/1 1
INACTIVE INGREDIENTS: POVIDONE; STARCH, CORN; STEARIC ACID; SODIUM STARCH GLYCOLATE TYPE A POTATO

Uline Acetaminophen Extra Strength

Active ingredient (in each tablet)

Acetaminophen 500 mg

Purpose

Pain reliever/fever reducer

Uses

Temporarily relieves minor aches and pains due to:

- headache
- muscular aches
- minor arthritis pain
- backache
- the common cold
- toothache
- premenstrual and menstrual cramps

Temporarily reduces fever.

Warnings

Liver warning:

This product contains acetaminophen. Severe liver damage may occur if you take:

- more than 4,000 mg in 24 hours, which is the maximum daily amount
- with other drugs containing acetaminophen
- 3 or more alcoholic drinks every day while using this product

Allergy alert:

Acetaminophen may cause severe skin reactions. Symptoms may include:

- skin reddening
- blisters
- rash

If a skin reaction occurs, stop use and seek medical help right away.

Do not use

- with any other drug containing acetaminophen (prescription or nonprescription). If you are not sure whether a drug

contains acetaminophen, ask a doctor or pharmacist.

- if you are allergic to acetaminophen or any of the inactive ingredients in this product.

Ask a doctor before use if you have

- liver disease

Ask a doctor or pharmacist before use if you have

- liver disease

Stop use and ask a doctor if

- pain gets worse or lasts for more than 10 days
- fever gets worse or lasts more than 3 days
- new symptoms occur
- redness or swelling is present

These could be signs of a serious condition.

If pregnant or breast-feeding,

ask a health professional before use.

Keep out of reach of children.

Overdose warning: In case of overdose, get medical help or contact a Poison Control Center right away (1-800-222-1222). Quick medical attention is critical for adults as well as for children even if you do not notice any signs or symptoms.

Directions

- do not use more than directed (see overdose warning)

Adults and children: (12 years and over)

Take 2 tablets every 6 while symptoms last. Do not take more than 6 tablets in 24 hours, unles directed by a doctor. Do not use for more than 10 days unless directed by a doctor.

Children under 12 years:

Ask a doctor.

Other information

- store at room temperature 59º-86ºF (15º-30ºC)
- tamper-evident sealed packets
- do not use any opened or torn packets

Inactive ingredients

corn starch*, hypromellose*, polyethylene glycol*, povidone (K-30)*, pregelatinized starch*, purified water*, sodium starch glycolate, stearic acid, titanium dioxide*

* May contain

Questions or comments?

1-800-295-5510

Uline Acetaminophen Extra Strength Label

ULINE

Tamper evident sealed packets:

Do not use if packet is open or torn.

This package is for households without young children

Acetaminophen

Pull to Open

Extra Strength

500 mg

• Pain Reliever

• Fever Reducer

50 Packets

2 tablets Each

Uline Acetaminohen Extra Strength Label

ULINE

Tamper evident sealed packets:

Do not use if packet is open or torn.

This package is for households without young children

Acetaminophen

Pull to Open

Extra Strength

500 mg

• Pain Reliever

• Fever Reducer

50 Packets

2 tablets Each

PACKAGE LABEL

ULINE

Tamper evident sealed packets:

Do not use if packet is open or torn.

This package is for households without young children

Acetaminophen

Pull to Open

Extra Strength

500 mg

• Pain Reliever

• Fever Reducer

50 Packets

2 tablets Each